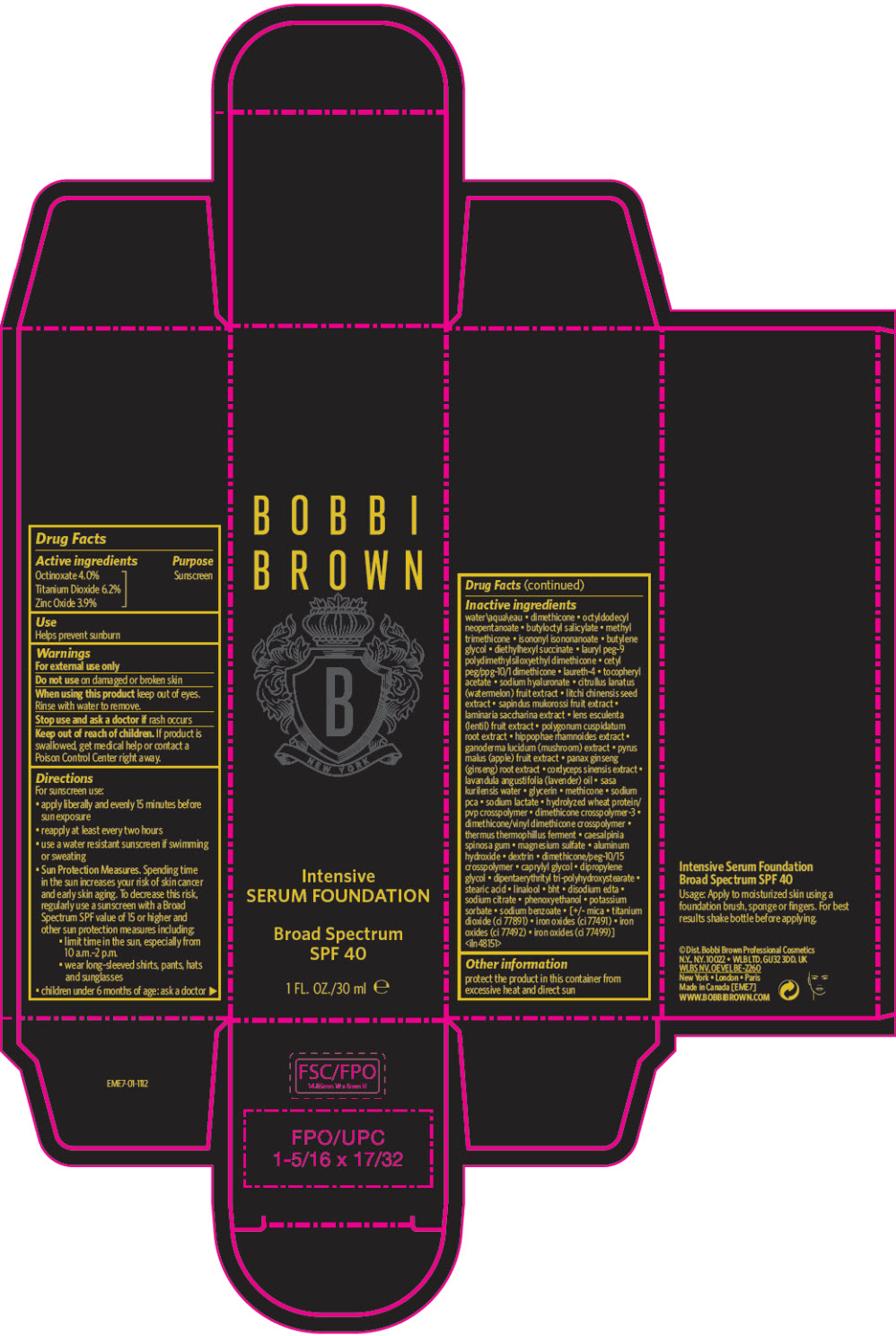 DRUG LABEL: BOBBI BROWN INTENSIVE SERUM FOUNDATION BROAD SPECTRUM SPF 40
NDC: 64141-031 | Form: LIQUID
Manufacturer: Bobbi Brown Professional Cosmetics Inc.
Category: otc | Type: HUMAN OTC DRUG LABEL
Date: 20241216

ACTIVE INGREDIENTS: OCTINOXATE 40 mg/1 mL; TITANIUM DIOXIDE 62 mg/1 mL; ZINC OXIDE 39 mg/1 mL
INACTIVE INGREDIENTS: SASA KURILENSIS WHOLE; GLYCERIN; METHICONE (20 CST); SODIUM PYRROLIDONE CARBOXYLATE; SODIUM LACTATE; HYDROLYZED WHEAT PROTEIN (ENZYMATIC; 3000 MW); DIMETHICONE CROSSPOLYMER (450000 MPA.S AT 12% IN CYCLOPENTASILOXANE); DIMETHICONE/VINYL DIMETHICONE CROSSPOLYMER (HARD PARTICLE); THERMUS THERMOPHILUS; CAESALPINIA SPINOSA WHOLE; MAGNESIUM SULFATE ANHYDROUS; ALUMINUM HYDROXIDE; DEXTRIN PALMITATE (CORN; 20000 MW); DIMETHICONE/PEG-10/15 CROSSPOLYMER; CAPRYLYL GLYCOL; DIPROPYLENE GLYCOL; DIPENTAERYTHRITYL TRI-POLYHYDROXYSTEARATE; STEARIC ACID; LINALOOL OXIDE; BUTYLATED HYDROXYTOLUENE; DISODIUM EDTA-COPPER; SODIUM CITRATE, UNSPECIFIED FORM; PHENOXYETHANOL; POTASSIUM SORBATE; SODIUM BENZOATE; MICA; FERRIC OXIDE RED; FERRIC OXIDE YELLOW; FERROSOFERRIC OXIDE; WATER; DIMETHICONE; OCTYLDODECYL NEOPENTANOATE; BUTYLOCTYL SALICYLATE; METHYL TRIMETHICONE; ISONONYL ISONONANOATE; BUTYLENE GLYCOL; DIETHYLHEXYL SUCCINATE; LAURYL PEG-9 POLYDIMETHYLSILOXYETHYL DIMETHICONE; CETYL PEG/PPG-10/1 DIMETHICONE (HLB 2); LAURETH-4; .ALPHA.-TOCOPHEROL ACETATE; HYALURONATE SODIUM; WATERMELON; LITCHI CHINENSIS SEED; SAPINDUS MUKOROSSI FRUIT; SACCHARINA LATISSIMA; LENS CULINARIS FRUIT; REYNOUTRIA JAPONICA ROOT; HIPPOPHAE RHAMNOIDES FRUIT; REISHI; APPLE; PANAX GINSENG ROOT OIL; OPHIOCORDYCEPS SINENSIS; LAVENDER OIL

BOBBI BROWN INTENSIVE SERUM FOUNDATION BROAD SPECTRUM SPF 40

Drug Facts

Active ingredients

Octinoxate 4.0%
Titanium Dioxide 6.2%
Zinc Oxide 3.9%

Purpose

Sunscreen

Use

Helps prevent sunburn

Warnings

For external use only

Do not use on damaged or broken skin

When using this product keep out of eyes.

Rinse with water to remove.

Stop use and ask a doctor if rash occurs

Keep out of reach of children. If product is swallowed, get medical help or contact a Poison Control Center right away.

Directions

For sunscreen use:

- apply liberally and evenly 15 minutes before sun exposure
- reapply at least every two hours
- use a water resistant sunscreen if swimming or sweating
- Sun Protection Measures. Spending time in the sun increases your risk of skin cancer and early skin aging. To decrease this risk, regularly use a sunscreen with a Broad Spectrum SPF value of 15 or higher and other sun protection measures including:
  - limit time in the sun, especially from 10 a.m.–2 p.m.
  - wear long-sleeved shirts, pants, hats and sunglasses
- children under 6 months of age: ask a doctor

Inactive ingredients

water\aqua\eau • dimethicone • octyldodecyl neopentanoate • butyloctyl salicylate • methyl trimethicone • isononyl isononanoate • butylene glycol • diethylhexyl succinate • lauryl peg-9 polydimethylsiloxyethyl dimethicone • cetyl peg/ppg-10/1 dimethicone • laureth-4 • tocopheryl acetate • sodium hyaluronate • citrullus lanatus (watermelon) fruit extract • litchi chinensis seed extract • sapindus mukorossi fruit extract • laminaria saccharina extract • lens esculenta (lentil) fruit extract • polygonum cuspidatum root extract • hippophae rhamnoides extract • ganoderma lucidum (mushroom) extract • pyrus malus (apple) fruit extract • panax ginseng (ginseng) root extract • cordyceps sinensis extract • lavandula angustifolia (lavender) oil • sasa kurilensis water • glycerin • methicone • sodium pca • sodium lactate • hydrolyzed wheat protein/ pvp crosspolymer • dimethicone crosspolymer-3 • dimethicone/vinyl dimethicone crosspolymer • thermus thermophillus ferment • caesalpinia spinosa gum • magnesium sulfate • aluminum hydroxide • dextrin • dimethicone/peg-10/15 crosspolymer • caprylyl glycol • dipropylene glycol • dipentaerythrityl tri-polyhydroxystearate • stearic acid • linalool • bht • disodium edta • sodium citrate • phenoxyethanol • potassium sorbate • sodium benzoate • [+/- mica • titanium dioxide (ci 77891) • iron oxides (ci 77491) • iron oxides (ci 77492) • iron oxides (ci 77499)] <iln48151>

Other information

protect the product in this container from excessive heat and direct sun

PRINCIPAL DISPLAY PANEL - 30 ml Tube Carton

BOBBI
BROWN

Intensive
SERUM FOUNDATION

Broad Spectrum
SPF 40

1 FL. OZ./30 ml e